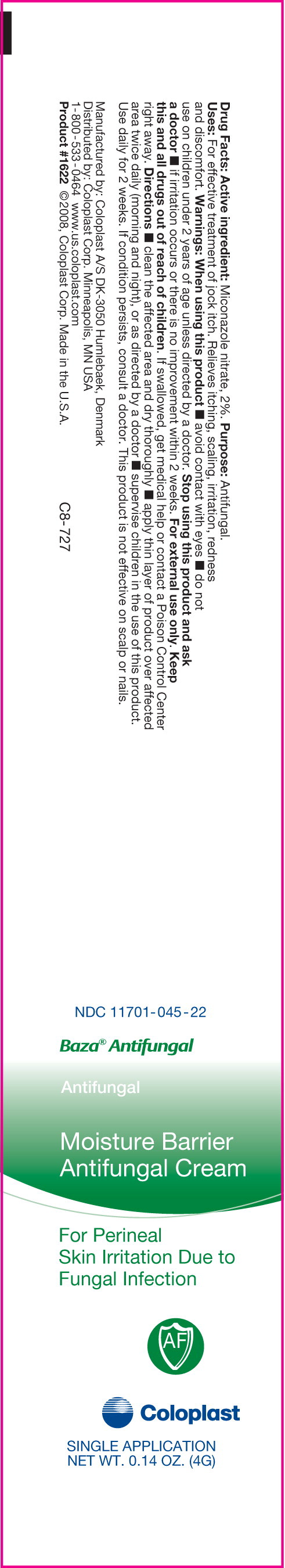 DRUG LABEL: Baza Antifungal
NDC: 11701-045 | Form: CREAM
Manufacturer: Coloplast Manufacturing US, LLC
Category: otc | Type: HUMAN OTC DRUG LABEL
Date: 20241226

ACTIVE INGREDIENTS: MICONAZOLE NITRATE 20 mg/1 g
INACTIVE INGREDIENTS: PETROLATUM; CETYL ALCOHOL; GLYCERYL MONOSTEARATE; BUTYLATED HYDROXYTOLUENE; COD LIVER OIL; .ALPHA.-TOCOPHEROL ACETATE, D-; LANOLIN; CETEARETH-6; STEARYL ALCOHOL; PROPYLENE GLYCOL; PEG-100 STEARATE; ZINC OXIDE; DIAZOLIDINYL UREA; WATER

Baza® Antifungal
Antifungal
Moisture Barrier
Antifungal
Cream

For Perineal
Skin Irritation Due to
Fungal Infection

Drug Facts

Active ingredient

Miconazole Nitrate, 2%

Purpose

Antifungal

INDICATIONS AND USAGE

Uses For effective treatment of jock itch. Relieves itching, scaling, irritation, redness and discomfort.

Warnings

When using this product

- avoid contact with eyes
- do not use on children under 2 years of age unless directed by a doctor.

STOP USE

Stop using this product and ask a doctor if irritation occurs or there is no improvement within 2 weeks.

For external use only.

KEEP OUT OF REACH OF CHILDREN

Keep this and all drugs out of reach of children. If swallowed, get medical help or contact a Poison Control Center right away.

Directions

- clean the affected area and dry thoroughly
- apply thin layer of product over affected area twice daily (morning and night), or as directed by a doctor
- supervise children in the use of this product.

Use daily for 2 weeks.

If condition persists, consult a doctor. This product is not effective on scalp or nails.

Inactive ingredients

BHT, cetearth-6, cetyl alcohol, cod liver oil, diazolidinyl urea, fragrance, glyceryl stearate, lanolin oil, PEG-100 stearate, petrolatum, polmethoxybicyclic oxazolidine, propylene glycol, water, stearyl alcohol, tocopheryl acetate, zinc oxide

See crimp for lot no. and expiration date

Manufactured by: Coloplast A/S DK-3050 Humlebaek, Denmark
Distributed by: Coloplast Corp. Minneapolis, MN 55411 U.S.A.
1-800-533-0464 www.us.coloplast.com
Product #1607 ©2008-7, Coloplast Corp.
Made in the U.S.A.

G8-664

PACKAGE LABEL

PRINCIPAL DISPLAY PANEL - NET WT. 5 OZ. (142 g)

NDC 11701-045-14

Baza® Antifungal

Antifungal

Moisture Barrier Antifungal Cream

For Perineal Skin Irritation Due to Fungal Infection

Coloplast

NET WT. 5 OZ. (142 g)